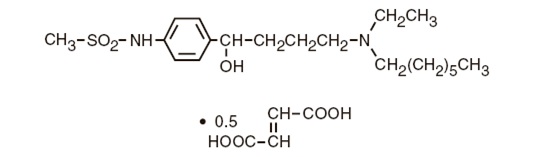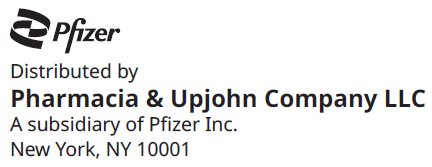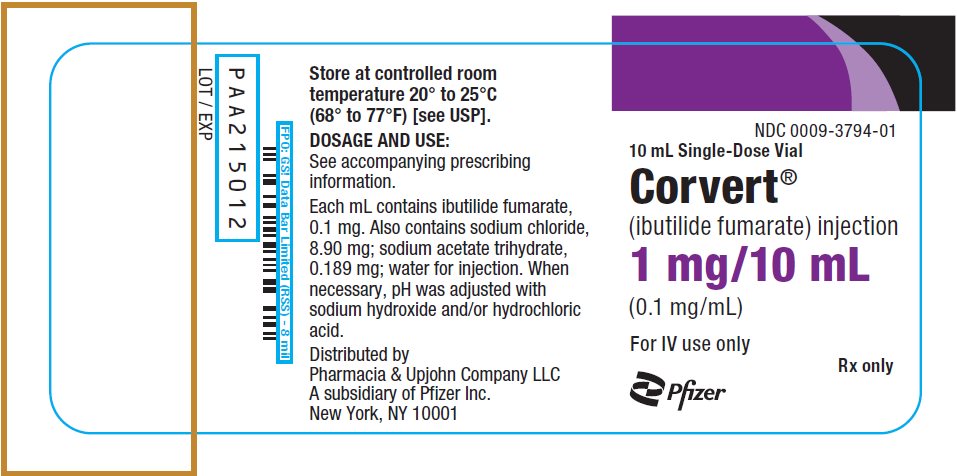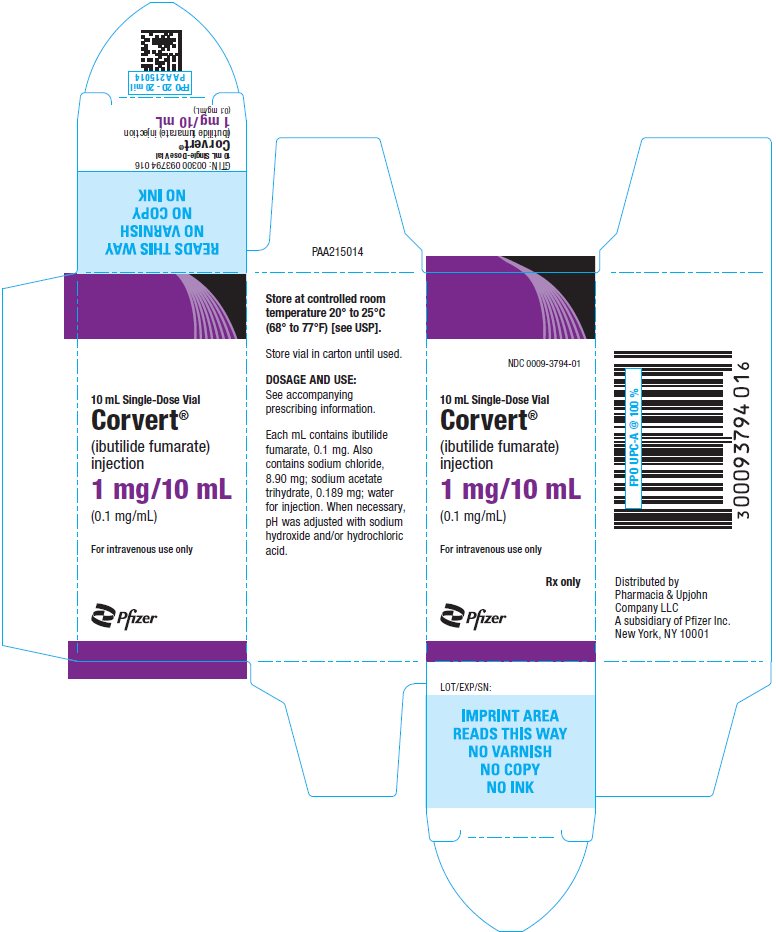 DRUG LABEL: Corvert
NDC: 0009-3794 | Form: INJECTION, SOLUTION
Manufacturer: Pharmacia & Upjohn Company LLC
Category: prescription | Type: HUMAN PRESCRIPTION DRUG LABEL
Date: 20240125

ACTIVE INGREDIENTS: IBUTILIDE FUMARATE 0.1 mg/1 mL
INACTIVE INGREDIENTS: SODIUM ACETATE 0.189 mg/1 mL; SODIUM CHLORIDE 8.9 mg/1 mL; HYDROCHLORIC ACID; WATER

Corvert®
(ibutilide fumarate) injection

For intravenous infusion only

DESCRIPTION

CORVERT Injection (ibutilide fumarate injection) is an antiarrhythmic drug with predominantly class III (cardiac action potential prolongation) properties according to the Vaughan Williams Classification. Each milliliter of CORVERT Injection contains 0.1 mg of ibutilide fumarate (equivalent to 0.087 mg ibutilide free base), 0.189 mg sodium acetate trihydrate, 8.90 mg sodium chloride, hydrochloric acid to adjust pH to approximately 4.6, and Water for Injection.

CORVERT Injection is an isotonic, clear, colorless, sterile aqueous solution.

Ibutilide fumarate has one chiral center, and exists as a racemate of the (+) and (−) enantiomers.

The chemical name for ibutilide fumarate is Methanesulfonamide, N-{4-{4-(ethylheptylamino)-1-hydroxybutyl}phenyl}, (+) (−), (E)-2-butenedioate (1:0.5) (hemifumarate salt). Its molecular formula is C22H38N2O5S, and its molecular weight is 442.62.

Ibutilide fumarate is a white to off-white powder with an aqueous solubility of over 100 mg/mL at pH 7 or lower.

The structural formula of ibutilide fumarate is represented below:

CLINICAL PHARMACOLOGY

Mechanism of Action:

CORVERT Injection prolongs action potential duration in isolated adult cardiac myocytes and increases both atrial and ventricular refractoriness in vivo, ie, class III electrophysiologic effects. Voltage clamp studies indicate that CORVERT, at nanomolar concentrations, delays repolarization by activation of a slow, inward current (predominantly sodium), rather than by blocking outward potassium currents, which is the mechanism by which most other class III antiarrhythmics act. These effects lead to prolongation of atrial and ventricular action potential duration and refractoriness, the predominant electrophysiologic properties of CORVERT in humans that are thought to be the basis for its antiarrhythmic effect.

Electrophysiologic Effects:

CORVERT produces mild slowing of the sinus rate and atrioventricular conduction. CORVERT produces no clinically significant effect on QRS duration at intravenous doses up to 0.03 mg/kg administered over a 10-minute period. Although there is no established relationship between plasma concentration and antiarrhythmic effect, CORVERT produces dose-related prolongation of the QT interval, which is thought to be associated with its antiarrhythmic activity. (See WARNINGS for relationship between QTc prolongation and torsades de pointes-type arrhythmias.) In a study in healthy volunteers, intravenous infusions of CORVERT resulted in prolongation of the QT interval that was directly correlated with ibutilide plasma concentration during and after 10-minute and 8-hour infusions. A steep ibutilide concentration/response (QT prolongation) relationship was shown. The maximum effect was a function of both the dose of CORVERT and the infusion rate.

Hemodynamic Effects:

A study of hemodynamic function in patients with ejection fractions both above and below 35% showed no clinically significant effects on cardiac output, mean pulmonary arterial pressure, or pulmonary capillary wedge pressure at doses of CORVERT up to 0.03 mg/kg.

Pharmacokinetics:

After intravenous infusion, ibutilide plasma concentrations rapidly decrease in a multiexponential fashion. The pharmacokinetics of ibutilide are highly variable among subjects. Ibutilide has a high systemic plasma clearance that approximates liver blood flow (about 29 mL/min/kg), a large steady-state volume of distribution (about 11 L/kg) in healthy volunteers, and minimal (about 40%) protein binding. Ibutilide is also cleared rapidly and highly distributed in patients being treated for atrial flutter or atrial fibrillation. The elimination half-life averages about 6 hours (range from 2 to 12 hours). The pharmacokinetics of ibutilide are linear with respect to the dose of CORVERT over the dose range of 0.01 mg/kg to 0.10 mg/kg. The enantiomers of ibutilide fumarate have pharmacokinetic properties similar to each other and to ibutilide fumarate.

The pharmacokinetics of CORVERT Injection in patients with atrial flutter or atrial fibrillation are similar regardless of the type of arrhythmia, patient age, sex, or the concomitant use of digoxin, calcium channel blockers, or beta blockers.

Metabolism and elimination:

In healthy male volunteers, about 82% of a 0.01 mg/kg dose of [^14C] ibutilide fumarate was excreted in the urine (about 7% of the dose as unchanged ibutilide) and the remainder (about 19%) was recovered in the feces.

Eight metabolites of ibutilide were detected in metabolic profiling of urine. These metabolites are thought to be formed primarily by ω-oxidation followed by sequential β-oxidation of the heptyl side chain of ibutilide. Of the eight metabolites, only the ω-hydroxy metabolite possesses class III electrophysiologic properties similar to that of ibutilide in an in vitro isolated rabbit myocardium model. The plasma concentrations of this active metabolite, however, are less than 10% of that of ibutilide.

Clinical Studies:

Treatment with intravenous ibutilide fumarate for acute termination of recent onset atrial flutter/fibrillation was evaluated in 466 patients participating in two randomized, double-blind, placebo-controlled clinical trials. Patients had had their arrhythmias for 3 hours to 90 days, were anticoagulated for at least 2 weeks if atrial fibrillation was present more than 3 days, had serum potassium of at least 4.0 mEq/L and QTc below 440 msec, and were monitored by telemetry for at least 24 hours. Patients could not be on class I or other class III antiarrhythmics (these had to be discontinued at least 5 half-lives prior to infusion) but could be on calcium channel blockers, beta blockers, or digoxin. In one trial, single 10-minute infusions of 0.005 to 0.025 mg/kg were tested in parallel groups (0.3 to 1.5 mg in a 60 kg person). In the second trial, up to two infusions of ibutilide fumarate were evaluated—the first 1.0 mg, the second given 10 minutes after completion of the first infusion, either 0.5 or 1.0 mg. In a third double-blind study, 319 patients with atrial fibrillation or atrial flutter of 3 hours to 45 days duration were randomized to receive single, 10-minute intravenous infusions of either sotalol (1.5 mg/kg) or CORVERT (1 mg or 2 mg). Among patients with atrial flutter, 53% receiving 1 mg ibutilide fumarate and 70% receiving 2 mg ibutilide fumarate converted, compared to 18% of those receiving sotalol. In patients with atrial fibrillation, 22% receiving 1 mg ibutilide fumarate and 43% receiving 2 mg ibutilide fumarate converted compared to 10% of patients receiving sotalol.

Patients in registration trials were hemodynamically stable. Patients with specific cardiovascular conditions such as symptomatic heart failure, recent acute myocardial infarction, and angina were excluded. About two thirds had cardiovascular symptoms, and the majority of patients had left atrial enlargement, decreased left ventricular ejection fraction, a history of valvular disease, or previous history of atrial fibrillation or flutter. Electrical cardioversion was allowed 90 minutes after the infusion was complete. Patients could be given other antiarrhythmic drugs 4 hours postinfusion.

Results of the first two studies are shown in the tables below. Conversion of atrial flutter/fibrillation usually (70% of those who converted) occurred within 30 minutes of the start of infusion and was dose related. The latest conversion seen was at 90 minutes after the start of the infusion. Most converted patients remained in normal sinus rhythm for 24 hours. Overall responses in these patients, defined as termination of arrhythmias for any length of time during or within 1 hour following completed infusion of randomized dose, were in the range of 43% to 48% at doses above 0.0125 mg/kg (vs 2% for placebo). Twenty-four hour responses were similar. For these atrial arrhythmias, ibutilide was more effective in patients with flutter than fibrillation (≥ 48% vs ≤ 40%).

PERCENT OF PATIENTS WHO CONVERTED (First Trial)
 |  |  | Ibutilide
 |  | Placebo | 0.005 mg/kg | 0.01 mg/kg | 0.015 mg/kg | 0.025 mg/kg
 | n | 41 | 41 | 40 | 38 | 40
Both | Initially [Percent of patients who converted within 70 minutes after the start of infusion.] | 2 | 12 | 33 | 45 | 48
Both | At 24 hours [Percent of patients who remained in sinus rhythm 24 hours after dosing.] | 2 | 12 | 28 | 42 | 43
Atrial flutter | Initially | 0 | 14 | 30 | 58 | 55
Atrial flutter | At 24 hours | 0 | 14 | 30 | 58 | 50
Atrial fibrillation | Initially | 5 | 10 | 35 | 32 | 40
Atrial fibrillation | At 24 hours | 5 | 10 | 25 | 26 | 35

PERCENT OF PATIENTS WHO CONVERTED (Second Trial)
 |  |  | Ibutilide
 |  | Placebo | 1.0 mg/0.5 mg | 1.0 mg/1.0 mg
 | n | 86 | 86 | 94
Both | Initially [Percent of patients who converted within 90 minutes after the start of infusion.] | 2 | 43 | 44
Both | At 24 hours [Percent of patients who remained in sinus rhythm 24 hours after dosing.] | 2 | 34 | 37
Atrial flutter | Initially | 2 | 48 | 63
Atrial flutter | At 24 hours | 2 | 45 | 59
Atrial fibrillation | Initially | 2 | 38 | 25
Atrial fibrillation | At 24 hours | 2 | 21 | 17

The numbers of patients who remained in the converted rhythm at the end of 24 hours were slightly less than those patients who converted initially, but the difference between conversion rates for ibutilide compared to placebo was still statistically significant. In long-term follow-up, approximately 40% of all patients remained recurrence free, usually with chronic prophylactic treatment, 400 to 500 days after acute treatment, regardless of the method of conversion.

Patients with more recent onset of arrhythmia had a higher rate of conversion. Response rates were 42% and 50% for patients with onset of atrial fibrillation/flutter for less than 30 days in the two efficacy studies compared to 16% and 31% in those with more chronic arrhythmias.

Ibutilide was equally effective in patients below and above 65 years of age and in men and women. Female patients constituted about 20% of patients in controlled studies.

Post-cardiac Surgery:

In a double-blind, parallel group study, 302 patients with atrial fibrillation (n=201) or atrial flutter (n=101) that occurred 1 to 7 days after coronary artery bypass graft or valvular surgery and lasted 1 hour to 3 days were randomized to receive two 10-minute infusions of placebo, or 0.25, 0.5 or 1 mg of ibutilide fumarate. Among patients with atrial flutter, conversion rates at 1.5 hours were: placebo, 4%; 0.25 mg ibutilide fumarate, 56%; 0.5 mg ibutilide fumarate, 61%; and 1 mg ibutilide fumarate, 78%. Among patients with atrial fibrillation, conversion rates at 1.5 hours were: placebo, 20%; 0.25 mg ibutilide fumarate, 28%; 0.5 mg ibutilide fumarate, 42%, and 1 mg ibutilide fumarate, 44%. The majority of patients (53% and 72% in the 0.5-mg and 1-mg dose groups, respectively) converted to sinus rhythm remained in sinus rhythm for 24 hours. Patients were not given other antiarrhythmic drugs within 24 hours of ibutilide fumarate infusion in this study.

INDICATIONS AND USAGE

CORVERT Injection is indicated for the rapid conversion of atrial fibrillation or atrial flutter of recent onset to sinus rhythm. Patients with atrial arrhythmias of longer duration are less likely to respond to CORVERT. The effectiveness of ibutilide has not been determined in patients with arrhythmias of more than 90 days in duration.

BOXED WARNING

LIFE-THREATENING ARRHYTHMIAS—APPROPRIATE TREATMENT ENVIRONMENT

CORVERT can cause potentially fatal arrhythmias, particularly sustained polymorphic ventricular tachycardia, usually in association with QT prolongation (torsades de pointes), but sometimes without documented QT prolongation. In registration studies, these arrhythmias, which require cardioversion, occurred in 1.7% of treated patients during, or within a number of hours of, use of CORVERT. These arrhythmias can be reversed if treated promptly (see WARNINGS, Proarrhythmia). It is essential that CORVERT be administered in a setting of continuous ECG monitoring and by personnel trained in identification and treatment of acute ventricular arrhythmias, particularly polymorphic ventricular tachycardia. Patients with atrial fibrillation of more than 2 to 3 days' duration must be adequately anticoagulated, generally for at least 2 weeks.

CHOICE OF PATIENTS

Patients with chronic atrial fibrillation have a strong tendency to revert after conversion to sinus rhythm (see CLINICAL STUDIES) and treatments to maintain sinus rhythm carry risks. Patients to be treated with CORVERT, therefore, should be carefully selected such that the expected benefits of maintaining sinus rhythm outweigh the immediate risks of CORVERT, and the risks of maintenance therapy, and are likely to offer an advantage compared with alternative management.

CONTRAINDICATIONS

CORVERT Injection is contraindicated in patients who have previously demonstrated hypersensitivity to ibutilide fumarate or any of the other product components.

WARNINGS

Proarrhythmia:

Like other antiarrhythmic agents, CORVERT Injection can induce or worsen ventricular arrhythmias in some patients. This may have potentially fatal consequences. Torsades de pointes, a polymorphic ventricular tachycardia that develops in the setting of a prolonged QT interval, may occur because of the effect CORVERT has on cardiac repolarization, but CORVERT can also cause polymorphic VT in the absence of excessive prolongation of the QT interval. In general, with drugs that prolong the QT interval, the risk of torsades de pointes is thought to increase progressively as the QT interval is prolonged and may be worsened with bradycardia, a varying heart rate, and hypokalemia. In clinical trials conducted in patients with atrial fibrillation and atrial flutter, those with QTc intervals >440 msec were not usually allowed to participate, and serum potassium had to be above 4.0 mEq/L. Although change in QTc was dose dependent for ibutilide, there was no clear relationship between risk of serious proarrhythmia and dose in clinical studies, possibly due to the small number of events. In clinical trials of intravenous ibutilide, patients with a history of congestive heart failure (CHF) or low left ventricular ejection fraction appeared to have a higher incidence of sustained polymorphic ventricular tachycardia (VT), than those without such underlying conditions; for sustained polymorphic VT the rate was 5.4% in patients with a history of CHF and 0.8% without it. There was also a suggestion that women had a higher risk of proarrhythmia, but the sex difference was not observed in all studies and was most prominent for nonsustained ventricular tachycardia. The incidence of sustained ventricular arrhythmias was similar in male (1.8%) and female (1.5%) patients, possibly due to the small number of events. CORVERT is not recommended in patients who have previously demonstrated polymorphic ventricular tachycardia (eg, torsades de pointes).

During registration trials, 1.7% of patients with atrial flutter or atrial fibrillation treated with CORVERT developed sustained polymorphic ventricular tachycardia requiring cardioversion. In these clinical trials, many initial episodes of polymorphic ventricular tachycardia occurred after the infusion of CORVERT was stopped but generally not more than 40 minutes after the start of the first infusion. There were, however, instances of recurrent polymorphic VT that occurred about 3 hours after the initial infusion. In two cases, the VT degenerated into ventricular fibrillation, requiring immediate defibrillation. Other cases were managed with cardiac pacing and magnesium sulfate infusions. Nonsustained polymorphic ventricular tachycardia occurred in 2.7% of patients and nonsustained monomorphic ventricular tachycardias occurred in 4.9% of the patients (see ADVERSE REACTIONS).

Proarrhythmic events must be anticipated. Skilled personnel and proper equipment, including cardiac monitoring equipment, intracardiac pacing facilities, a cardioverter/defibrillator, and medication for treatment of sustained ventricular tachycardia, including polymorphic ventricular tachycardia, must be available during and after administration of CORVERT. Before treatment with CORVERT, hypokalemia and hypomagnesemia should be corrected to reduce the potential for proarrhythmia. Patients should be observed with continuous ECG monitoring for at least 4 hours following infusion or until QTc has returned to baseline. Longer monitoring is required if any arrhythmic activity is noted. Management of polymorphic ventricular tachycardia includes discontinuation of ibutilide, correction of electrolyte abnormalities, especially potassium and magnesium, and overdrive cardiac pacing, electrical cardioversion, or defibrillation. Pharmacologic therapies include magnesium sulfate infusions. Treatment with antiarrhythmics should generally be avoided.

PRECAUTIONS

General

Antiarrhythmics:

Class Ia antiarrhythmic drugs (Vaughan Williams Classification), such as disopyramide, quinidine, and procainamide, and other class III drugs, such as amiodarone and sotalol, should not be given concomitantly with CORVERT Injection or within 4 hours postinfusion because of their potential to prolong refractoriness. In the clinical trials, class I or other class III antiarrhythmic agents were withheld for at least 5 half-lives prior to ibutilide infusion and for 4 hours after dosing, but thereafter were allowed at the physician's discretion.

Other drugs that prolong the QT interval:

The potential for proarrhythmia may increase with the administration of CORVERT Injection to patients who are being treated with drugs that prolong the QT interval, such as phenothiazines, tricyclic antidepressants, tetracyclic antidepressants, and certain antihistamine drugs (H1 receptor antagonists).

Heart block:

Of the nine (1.5%) ibutilide-treated patients with reports of reversible heart block, five had first degree, three had second degree, and one had complete heart block.

Laboratory Test Interactions:

None known.

Drug Interactions:

No specific pharmacokinetic or other formal drug interaction studies were conducted.

Digoxin:

Supraventricular arrhythmias may mask the cardiotoxicity associated with excessive digoxin levels. Therefore, it is advisable to be particularly cautious in patients whose plasma digoxin levels are above or suspected to be above the usual therapeutic range. Coadministration of digoxin did not have effects on either the safety or efficacy of ibutilide in the clinical trials.

Calcium channel blocking agents:

Coadministration of calcium channel blockers did not have any effect on either the safety or efficacy of ibutilide in the clinical trials.

Beta-adrenergic blocking agents:

Coadministration of beta-adrenergic blocking agents did not have any effect on either the safety or efficacy of ibutilide in the clinical trials.

Carcinogenesis, Mutagenesis, Impairment of Fertility:

No animal studies have been conducted to determine the carcinogenic potential of CORVERT; however, it was not genotoxic in a battery of assays, (Ames assay, mammalian cell forward gene mutation assay, unscheduled DNA synthesis assay, and mouse micronucleus assay). Similarly, no drug-related effects on fertility or mating were noted in a reproductive study in rats in which ibutilide was administered orally to both sexes up to doses of 20 mg/kg/day. On a mg/m^2 basis, corrected for 3% bioavailability, the highest dose tested was approximately four times the maximum recommended human dose (MRHD).

Pregnancy:

Ibutilide administered orally was teratogenic (abnormalities included adactyly, interventricular septal defects, and scoliosis) and embryocidal in reproduction studies in rats. On a mg/m^2 basis, corrected for the 3% oral bioavailability, the "no adverse effect dose" (5 mg/kg/day given orally) was approximately the same as the maximum recommended human dose (MRHD); the teratogenic dose (20 mg/kg/day given orally) was about four times the MRHD on a mg/m^2 basis, or 16 times the MRHD on a mg/kg basis. CORVERT should not be administered to a pregnant woman unless clinical benefit outweighs potential risk to the fetus.

Nursing Mothers:

The excretion of ibutilide into breast milk has not been studied; accordingly, breastfeeding should be discouraged during therapy with CORVERT.

Pediatric Use:

Clinical trials with CORVERT in patients with atrial fibrillation and atrial flutter did not include anyone under the age of 18. Safety and effectiveness of ibutilide in pediatric patients has not been established.

Geriatric Use:

Clinical studies of ibutilide fumarate (involving 586 patients) did not include sufficient numbers of subjects less than age 65 (45%) to determine whether they respond differently from older subjects. Other reported clinical experience has not identified differences in responses between the elderly and younger patients. In general, dose selection for an elderly patient should be cautious, usually starting at the low end of the dosing range, reflecting the greater frequency of decreased hepatic, renal, or cardiac function, and of concomitant disease or other drug therapy.

Use in Patients With Hepatic or Renal Dysfunction:

The safety, effectiveness, and pharmacokinetics of CORVERT have not been established in patients with hepatic or renal dysfunction. However, it is unlikely that dosing adjustments would be necessary in patients with compromised renal or hepatic function based on the following considerations: (1) CORVERT is indicated for rapid intravenous therapy (duration ≤ 30 minutes) and is dosed to a known, well-defined pharmacologic action (termination of arrhythmia) or to a maximum of two 10-minute infusions; (2) less than 10% of the dose of CORVERT is excreted unchanged in the urine; and (3) drug distribution appears to be one of the primary mechanisms responsible for termination of the pharmacologic effect. Nonetheless, patients with abnormal liver function should be monitored by telemetry for more than the 4-hour period generally recommended.

In 285 patients with atrial fibrillation or atrial flutter who were treated with CORVERT, the clearance of ibutilide was independent of renal function, as assessed by creatinine clearance (range 21 to 140 mL/min).

ADVERSE REACTIONS

CORVERT Injection was generally well tolerated in clinical trials. Of the 586 patients with atrial fibrillation or atrial flutter who received CORVERT in phase II/III studies, 149 (25%) reported medical events related to the cardiovascular system, including sustained polymorphic ventricular tachycardia (1.7%) and nonsustained polymorphic ventricular tachycardia (2.7%).

Other clinically important adverse events with an uncertain relationship to CORVERT include the following (0.2% represents one patient): sustained monomorphic ventricular tachycardia (0.2%), nonsustained monomorphic ventricular tachycardia (4.9%), AV block (1.5%), bundle branch block (1.9%), ventricular extrasystoles (5.1%), supraventricular extrasystoles (0.9%), hypotension/postural hypotension (2.0%), bradycardia/sinus bradycardia (1.2%), nodal arrhythmia (0.7%), congestive heart failure (0.5%), tachycardia/sinus tachycardia/supraventricular tachycardia (2.7%), idioventricular rhythm (0.2%), syncope (0.3%), and renal failure (0.3%). The incidence of these events, except for syncope, was greater in the group treated with CORVERT than in the placebo group.

Another adverse reaction that may be associated with the administration of CORVERT was nausea, which occurred with a frequency greater than 1% more in ibutilide-treated patients than those treated with placebo.

The medical events reported for more than 1% of the placebo- and ibutilide-treated patients are shown in the following Table.

Treatment-Emergent Medical Events With Frequency of More Than 1% and Higher Than That of Placebo
Event | Placebo N=127 |  | All Ibutilide N=586
Event | Patients |  | Patients
Event | n | % | n | %
CARDIOVASCULAR
Ventricular extrasystoles | 1 | 0.8 | 30 | 5.1
Nonsustained monomorphic VT | 1 | 0.8 | 29 | 4.9
Nonsustained polymorphic VT | — | — | 16 | 2.7
Hypotension | 2 | 1.6 | 12 | 2.0
Bundle branch block | — | — | 11 | 1.9
Sustained polymorphic VT | — | — | 10 | 1.7
AV block | 1 | 0.8 | 9 | 1.5
Hypertension | — | — | 7 | 1.2
QT segment prolonged | — | — | 7 | 1.2
Bradycardia | 1 | 0.8 | 7 | 1.2
Palpitation | 1 | 0.8 | 6 | 1.0
Tachycardia | 1 | 0.8 | 16 | 2.7
GASTROINTESTINAL
Nausea | 1 | 0.8 | 11 | 1.9
CENTRAL NERVOUS SYSTEM
Headache | 4 | 3.1 | 21 | 3.6

In the post-cardiac surgery study (see CLINICAL STUDIES), similar types of medical events were reported. In the 1 mg ibutilide fumarate treatment group (N=70), 2 patients (2.9%) developed sustained polymorphic ventricular tachycardia and 2 other patients (2.9%) developed nonsustained polymorphic ventricular tachycardia. Polymorphic ventricular tachycardia was not reported in the 73 patients in the 0.5 mg dose group or in the 75 patients in the 0.25 mg dose group.

OVERDOSAGE

Acute Experience in Animals:

Acute overdose in animals results in CNS toxicity; notably, CNS depression, rapid gasping breathing, and convulsions. The intravenous median lethal dose in the rat was more than 50 mg/kg which is, on a mg/m^2 basis, at least 250 times the maximum recommended human dose.

Human Experience:

In the registration trials with CORVERT Injection, four patients were unintentionally overdosed. The largest dose was 3.4 mg administered over 15 minutes. One patient (0.025 mg/kg) developed increased ventricular ectopy and monomorphic ventricular tachycardia, another patient (0.032 mg/kg) developed AV block—3rd degree and nonsustained polymorphic VT, and two patients (0.038 and 0.020 mg/kg) had no medical event reports. Based on known pharmacology, the clinical effects of an overdosage with ibutilide could exaggerate the expected prolongation of repolarization seen at usual clinical doses. Medical events (eg, proarrhythmia, AV block) that occur after the overdosage should be treated with measures appropriate for that condition.

DOSAGE AND ADMINISTRATION

The recommended dose based on controlled trials (see CLINICAL STUDIES) is outlined in the Table below. Ibutilide infusion should be stopped as soon as the presenting arrhythmia is terminated or in the event of sustained or nonsustained ventricular tachycardia, or marked prolongation of QT or QTc.

Recommended Dose of CORVERT Injection
Patient Weight | Initial Infusion (over 10 minutes) | Second Infusion
60 kg (132 lb) or more | One vial (1 mg ibutilide fumarate) | If the arrhythmia does not terminate within 10 minutes after the end of the initial infusion, a second 10-minute infusion of equal strength may be administered 10 minutes after completion of the first infusion.
Less than 60 kg (132 lb) | 0.1 mL/kg (0.01 mg/kg ibutilide fumarate) | If the arrhythmia does not terminate within 10 minutes after the end of the initial infusion, a second 10-minute infusion of equal strength may be administered 10 minutes after completion of the first infusion.

In a trial comparing ibutilide and sotalol (see CLINICAL STUDIES), 2 mg ibutilide fumarate administered as a single infusion to patients weighing more than 60 kg was also effective in terminating atrial fibrillation or atrial flutter.

In the post-cardiac surgery study (see CLINICAL STUDIES), one or two intravenous infusions of 0.5 mg (0.005 mg/kg per dose for patients weighing less than 60 kg) was effective in terminating atrial fibrillation or atrial flutter.

Patients should be observed with continuous ECG monitoring for at least 4 hours following infusion or until QTc has returned to baseline. Longer monitoring is required if any arrhythmic activity is noted. Skilled personnel and proper equipment (see WARNINGS, Proarrhythmia), such as a cardioverter/defibrillator, and medication for treatment of sustained ventricular tachycardia, including polymorphic ventricular tachycardia, must be available during administration of CORVERT and subsequent monitoring of the patient.

Dilution:

CORVERT Injection may be administered undiluted or diluted in 50 mL of diluent. CORVERT may be added to 0.9% Sodium Chloride Injection or 5% Dextrose Injection before infusion. The contents of one 10 mL vial (0.1 mg/mL) may be added to a 50 mL infusion bag to form an admixture of approximately 0.017 mg/mL ibutilide fumarate. Parenteral drug products should be inspected visually for particulate matter and discoloration prior to administration whenever solution and container permit.

Compatibility and Stability:

The following diluents are compatible with CORVERT Injection (0.1 mg/mL):

5% Dextrose Injection
0.9% Sodium Chloride Injection

The following intravenous solution containers are compatible with admixtures of CORVERT Injection (0.1 mg/mL):

polyvinyl chloride plastic bags
polyolefin bags

Admixtures of the product, with approved diluents, are chemically and physically stable for 24 hours at room temperature (15° to 30° C or 59° to 86° F) and for 48 hours at refrigerated temperatures (2° to 8°C or 36° to 46°F). Strict adherence to the use of aseptic technique during the preparation of the admixture is recommended in order to maintain sterility.

HOW SUPPLIED

CORVERT Injection (ibutilide fumarate injection) is supplied as an acetate-buffered isotonic solution at a concentration of 0.1 mg/mL that has been adjusted to approximately pH 4.6 in 10 mL clear glass, single-dose, flip-top vials.

Single-dose 10 mL vial, 1 mg /10 mL (0.1 mg/mL) NDC 0009-3794-01

STORAGE AND HANDLING

Store at controlled room temperature 20° to 25°C (68° to 77°F) [see USP]. Store vial in carton until used.

LAB-0129-5.0

Revised November 2023

PRINCIPAL DISPLAY PANEL - 10 mL Single-Dose Vial Label

NDC 0009-3794-01

10 mL Single-Dose Vial

Corvert®
(ibutilide fumarate) injection

1 mg/10 mL

(0.1 mg/mL)

For IV use only

Rx only

Pfizer

PRINCIPAL DISPLAY PANEL - 10 mL Vial Carton

NDC 0009-3794-01

10 mL Single-Dose Vial

Corvert®
(ibutilide fumarate)
injection

1 mg/10 mL

(0.1 mg/mL)

For intravenous use only

Rx only

Pfizer